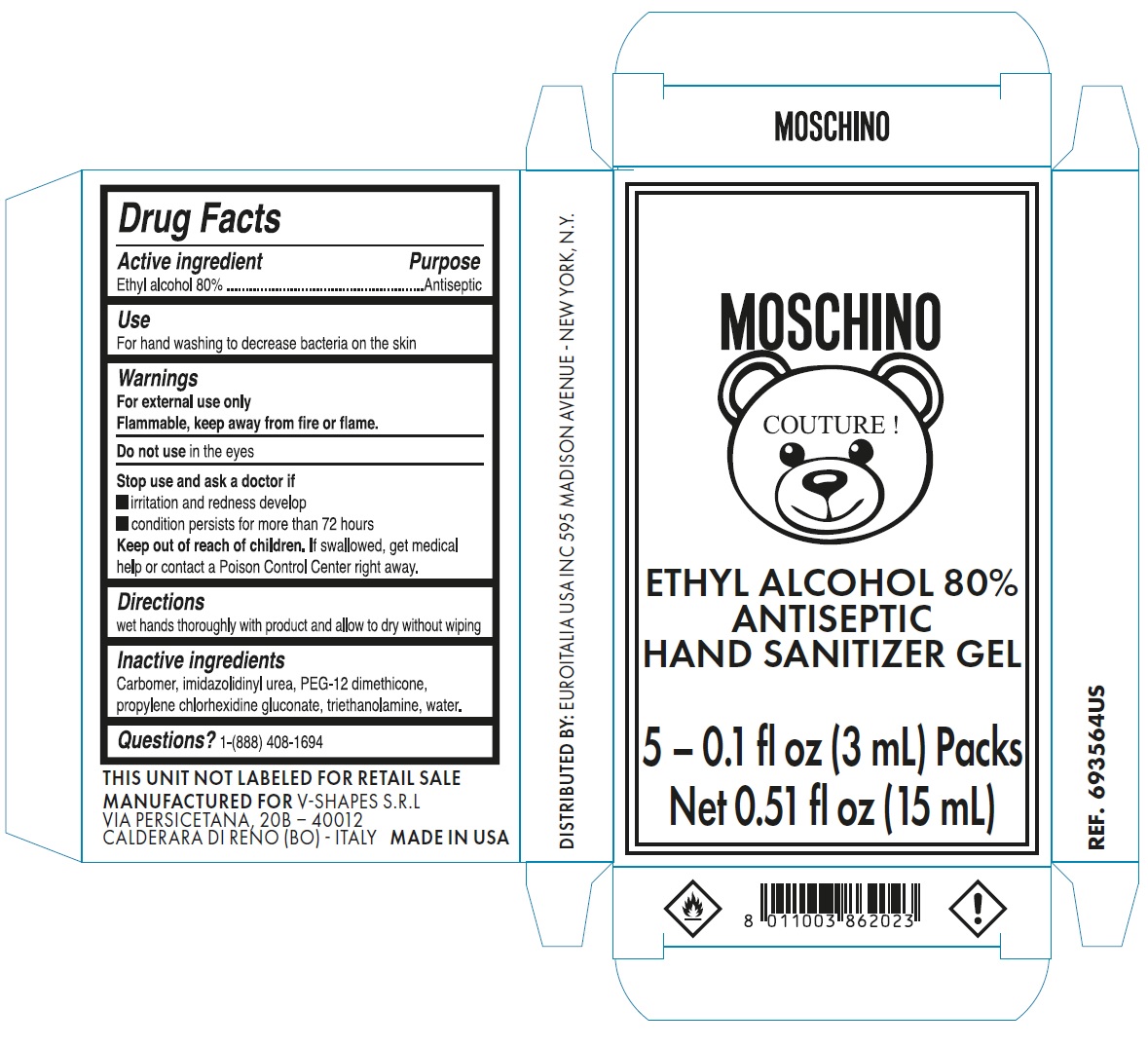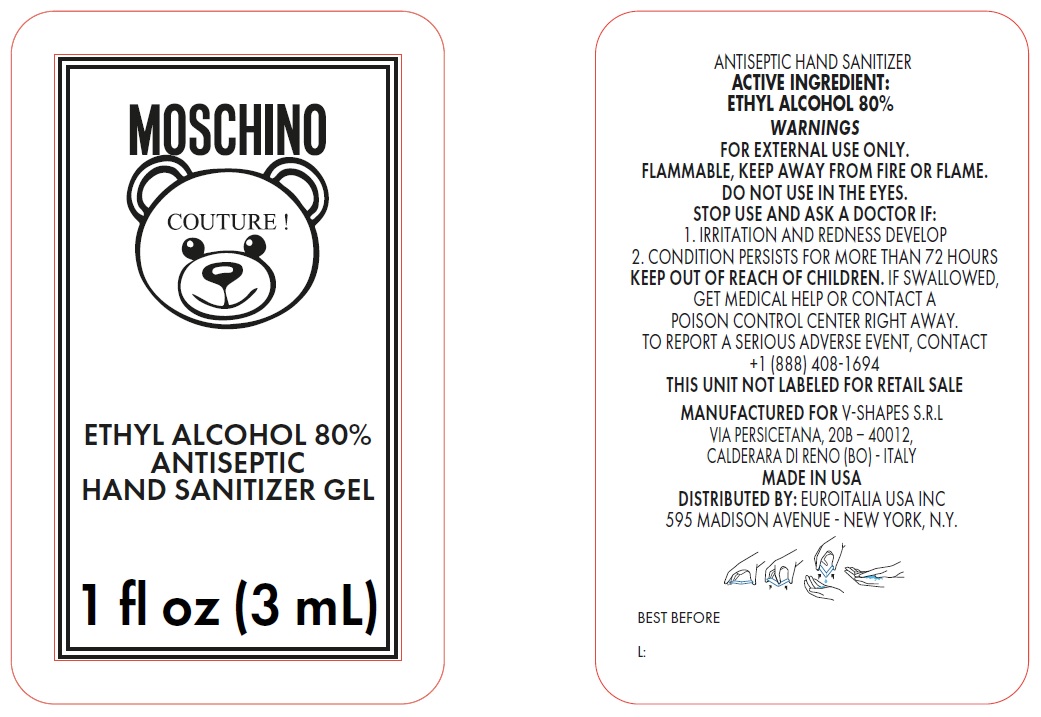 DRUG LABEL: Antiseptic Hand sanitizer MOSCHINO
NDC: 74785-002 | Form: GEL
Manufacturer: V-SHAPES SRL
Category: otc | Type: HUMAN OTC DRUG LABEL
Date: 20200728

ACTIVE INGREDIENTS: ALCOHOL 0.8 mL/1 mL
INACTIVE INGREDIENTS: CARBOMER HOMOPOLYMER, UNSPECIFIED TYPE; IMIDUREA; PEG-12 DIMETHICONE (300 CST); TROLAMINE; WATER

Antiseptic Hand sanitizer MOSCHINO

Active ingredient

Ethyl alcohol 80%

Purpose

Antiseptic

Use

For hand washing to decrease bacteria on the skin

Warnings

For external use only

Flammable, keep away from fire or flame.

Do not use

in the eyes

Stop use and ask a doctor if

- irritation and redness develop
- condition persists for more than 72 hours

Keep out of reach of children.

If swallowed, get medical help or contact a Poison Control Center right away.

Directions

wet hands thoroughly with product and allow to dry without wiping

Inactive ingredients

Carbomer, imidazolidinyl urea, PEG-12 dimethicone, propylene chlorhexidine gluconate, triethanolamine, water.

Questions?

1-(888) 408-1694